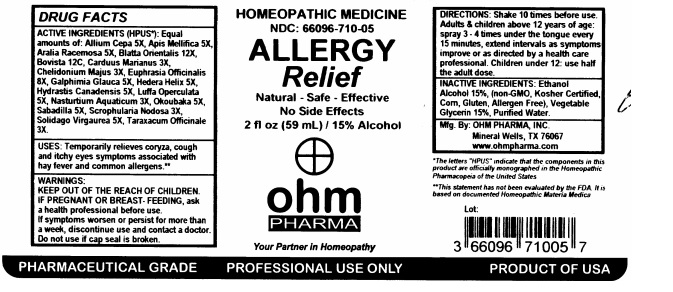 DRUG LABEL: Allergy Relief
NDC: 66096-710 | Form: LIQUID
Manufacturer: OHM PHARMA INC.
Category: homeopathic | Type: HUMAN OTC DRUG LABEL
Date: 20211229

ACTIVE INGREDIENTS: ONION 5 [hp_X]/59 mL; APIS MELLIFERA 5 [hp_X]/59 mL; ARALIA RACEMOSA ROOT 5 [hp_X]/59 mL; BLATTA ORIENTALIS 12 [hp_X]/59 mL; LYCOPERDON UTRIFORME FRUITING BODY 12 [hp_C]/59 mL; MILK THISTLE 3 [hp_X]/59 mL; CHELIDONIUM MAJUS 3 [hp_X]/59 mL; EUPHRASIA STRICTA 8 [hp_X]/59 mL; GALPHIMIA GLAUCA FLOWERING TOP 5 [hp_X]/59 mL; HEDERA HELIX FLOWERING TWIG 5 [hp_X]/59 mL; GOLDENSEAL 5 [hp_X]/59 mL; LUFFA OPERCULATA FRUIT 5 [hp_X]/59 mL; NASTURTIUM OFFICINALE 3 [hp_X]/59 mL; OKOUBAKA AUBREVILLEI BARK 5 [hp_X]/59 mL; SCHOENOCAULON OFFICINALE SEED 5 [hp_X]/59 mL; SCROPHULARIA NODOSA 3 [hp_X]/59 mL; SOLIDAGO VIRGAUREA FLOWERING TOP 5 [hp_X]/59 mL; TARAXACUM OFFICINALE 3 [hp_X]/59 mL
INACTIVE INGREDIENTS: ALCOHOL; GLYCERIN; WATER

ACTIVE INGREDIENT

ACTIVE INGERDIENTS (HPUS*): Equal amounts of: Allium Cepa 5X, Apis Mellifica 5X, Aralia Racemosa 5X, Blatta Orientalis 12X, Bovista 12C, Carduus Marianus 3X, Chelidonium Majus 3X, Euphrasia Officinalis 8X, Galphimia Glauca 5X, Hedera Helix 5X, Hydrastis Canadensis 5X, Luffa Operculata 5X, Nasturtium Aquaticum 3X, Okoubaka 5X, Sabadilla 5X, Scrophularia Nodosa 3X, Solidago Virgaurea 5X, Taraxacum Officinale 3X.

*The letters "HPUS" indicate that the components in this product are officially monographed in the Homeopathic Pharmacopeia of the United States.

INDICATIONS AND USAGE

USES: Temporarily relieves coryza, cough and itchy eyes symptoms associated with hay fever and common allergens.**

**This statement has not been evaluated by the FDA. It is based on documented Homeopathic Materia Medica.

WARNINGS:

KEEP OUT OF THE REACH OF CHILDREN IF PREGNANT OR BREAST - FEEDING, ask a health professional before use. If symptons worsen or persist for more than a week, discontinue use and contact a doctor. Do not use if cap seal is broken.

KEEP OUT OF THE REACH OF CHILDREN

DOSAGE AND ADMINISTRATION

DIRECTIONS: Shake 10 times before use. Adults & children above 12 years of age: spray 3 - 4 times under the tongue every 15 minutes, extend intervals as symptoms improve or as directed by a health care professional. Children under 12: use half the adults dose.

INACTIVE INGREDIENT

INACTIVE INGREDIENTS: Ethanol Alcohol 15%, (non-GMO, Kosher Certified, Corn, Gluten, Allergen Free), Vegetable Glycerin 15%, Purified Water.

PACKAGE LABEL

HOMEOPATHIC MEDICINE

NDC: 66096-710-05

ALLERGY

RELIEF

Natural - Safe - Effective

No Side Effects

2 fl oz (59 ml) / 15% Alcohol

PURPOSE

Natural - Safe - Effective

No Side Effects